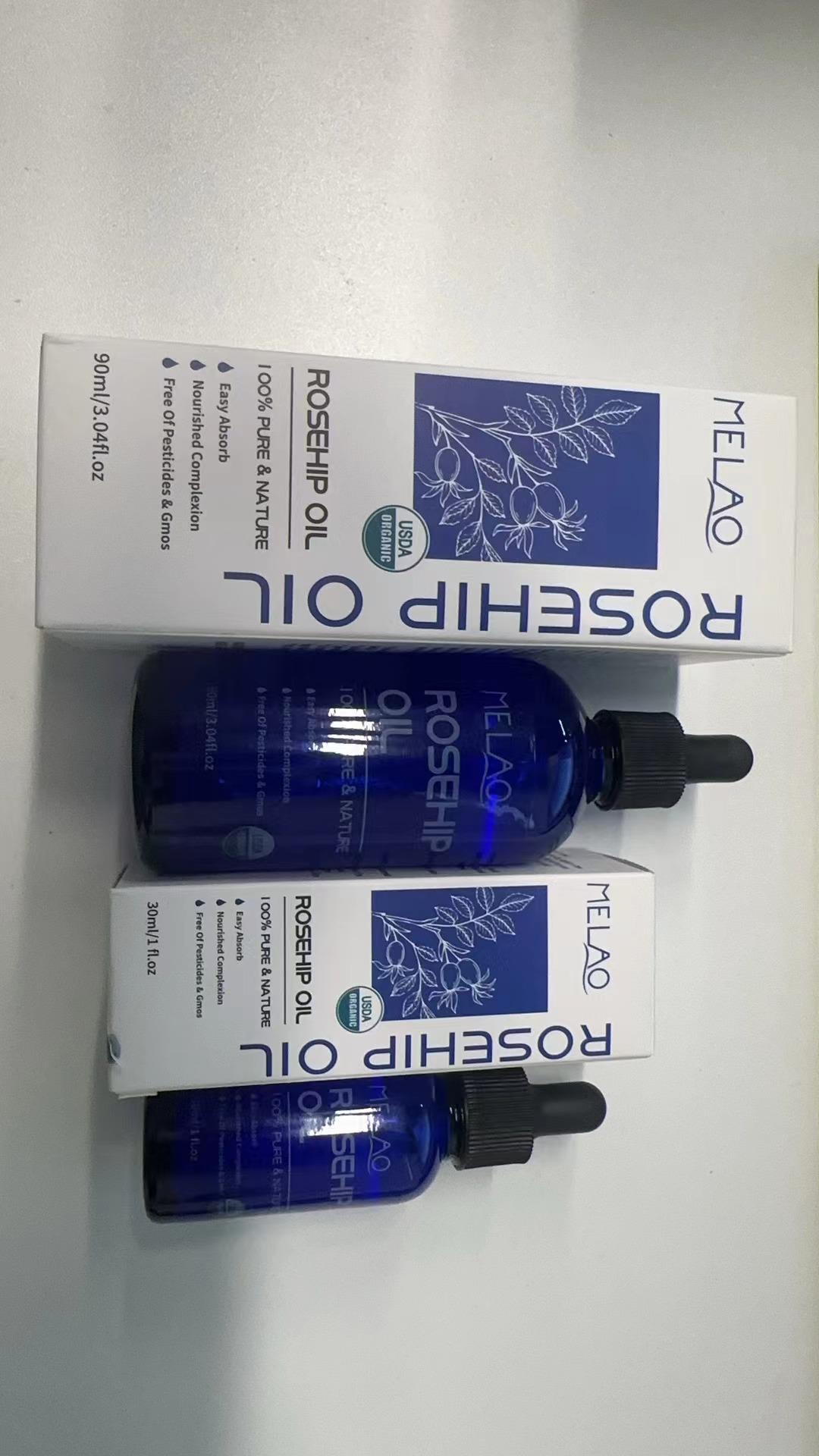 DRUG LABEL: ROSEHIP Oil
NDC: 83566-568 | Form: LIQUID
Manufacturer: Guangzhou Yilong Cosmetics Co., Ltd
Category: otc | Type: HUMAN OTC DRUG LABEL
Date: 20240807

ACTIVE INGREDIENTS: ROSA CANINA FRUIT OIL 95 g/100 g
INACTIVE INGREDIENTS: ROSA CANINA FLOWER OIL 5 g/100 g

Active ingredients

Rosa Canina Fruit Oil 95%

Purpose

Moisture

Uses

Step 1: Clean and thoroughly dry the skin.
Step 2: Twist the bottle cap to open the product.
Step 3: Gently apply to the skin or other desired areas.

Warnings

For external use only.

Stop use and ask a doctor if

rash occurs.

Do not use

on damaged or broken skin.

When using this product

keep out of eyes. Rinse withwater to remove.

Keep out of reach of children.

If swallowed, get medical help or contact a Poison Control Center right away.

DOSAGE

Squeeze out an appropriate amount of sunscreen and spread evenly on skin.

Inactive ingredients

Rosa Canina flower Oil5%